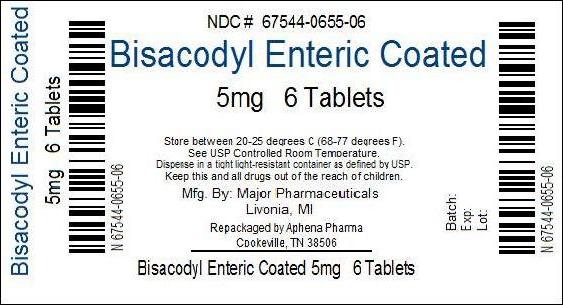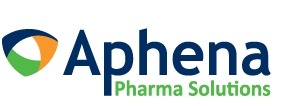 DRUG LABEL: Bisacodyl
NDC: 67544-655 | Form: TABLET, COATED
Manufacturer: Aphena Pharma Solutions - Tennessee, LLC
Category: otc | Type: HUMAN OTC DRUG LABEL
Date: 20191223

ACTIVE INGREDIENTS: BISACODYL 5 mg/1 1
INACTIVE INGREDIENTS: ACACIA; CALCIUM SULFATE ANHYDROUS; ANHYDROUS LACTOSE; CARNAUBA WAX; SILICON DIOXIDE; STARCH, CORN; D&C YELLOW NO. 10; FD&C YELLOW NO. 6; GELATIN, UNSPECIFIED; MAGNESIUM STEARATE; MICROCRYSTALLINE CELLULOSE; AMMONIUM NONOXYNOL-4 SULFATE; SHELLAC; SODIUM STARCH GLYCOLATE TYPE A POTATO; STEARIC ACID; TALC; TITANIUM DIOXIDE; Polyvinyl Acetate Phthalate

Bisacodyl Enteric Coated Tablet

Active ingredient(s)

Bisacodyl 5mg

Purpose

Stimulant laxative

Use(s)

-relieves occasional constipation and irregularity

-this product generally produces bowel movement in 6 to 12 hours

Warnings

Do not use if you cannot swallow without chewing

Ask a doctor before use if

-you have a sudden change in bowel habits that lasts more than 2 weeks

-stomach pain, nausea or vomiting

When using this product

-do not use within 1 hour after taking an antacid or milk

-do not chew or crush tablet(s)

-you may have stomach discomfort, faintness or cramps

Stop use and ask a doctor if

-you have rectal bleeding or fail to have a bowel movement after use of a laxative. These could be signs of a serious condition.

-you need to use a laxative for more than 1 week

Pregnancy/Breastfeeding

ask a health professions before use.

Keep out of reach of children. In case of overdose, get medical help or contact a Poison Control Center right away.

Directions

-take with a glass of water

adults and children 12 years and over- take 1 to 3 tablets in a single daily dose

children 6 to under 12 years of age - take 1 tablet in a single daily dose

children under 6 years of age - ask a doctor

Other information

Repackaged by Aphena Pharma Solutions - TN.
See Repackaging Information for available configurations.

Storage

-store at 25 degrees C (77 degrees F) excursions permitted between 15 degrees-30 degrees C (59 degrees-86 degrees F)

-use by expiration date on package

-protect from excessive humidity

Inactive ingredients

acacia, bees wax, calcium sulfate, carnauba wax, cellulose, corn starch, D&C Yellow No. 10 lake, FD&C Yellow No. 6 lake, gelatin, lactose, magnesium stearate, pharmaceutical glaze, polyvinyl acetate phthalate, silica gel, sodium starch glycolate, stearinc acid, sugar, talc, titanium dioxide.

Questions

To Report Adverse Drug Event call: (800) 616-2471

Repackaging Information

Please reference the Product Characteristics section listed below for a description of individual tablets or capsules. This drug product has been received by Aphena Pharma - TN in a manufacturer or distributor packaged configuration and repackaged in full compliance with all applicable cGMP regulations. The package configurations available from Aphena are listed below:

Count | 4mg
04 | 67544-655-04
06 | 67544-655-06

Store between 20°-25°C (68°-77°F). See USP Controlled Room Temperature. Dispense in a tight light-resistant container as defined by USP. Keep this and all drugs out of the reach of children.

Repackaged by:
Cookeville, TN 38506
20130612AW

PRINCIPAL DISPLAY PANEL - 5mg

NDC 67544-655 - Bisacodyl 5mg